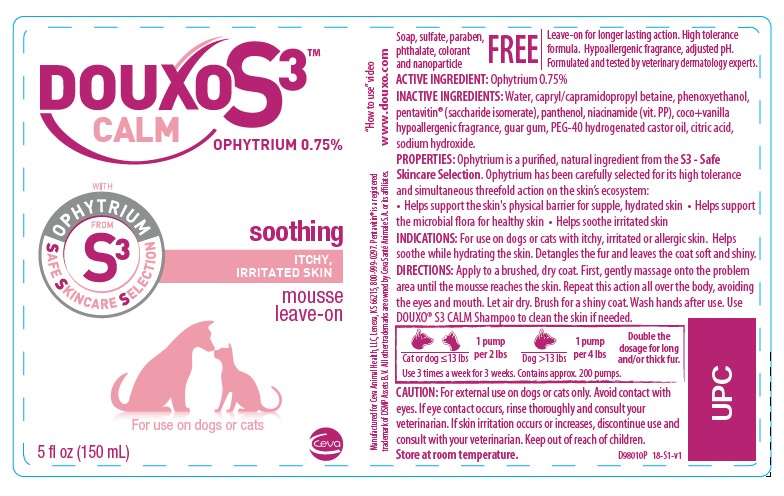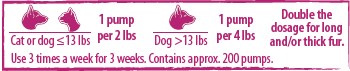 DRUG LABEL: DOUXO S3
NDC: 13744-150 | Form: LIQUID
Manufacturer: Ceva Sante Animale
Category: animal | Type: OTC ANIMAL DRUG LABEL
Date: 20250312

ACTIVE INGREDIENTS: OPHIOPOGON JAPONICUS ROOT 7.5 mg/1 mL
INACTIVE INGREDIENTS: SACCHARIDE ISOMERATE; PANTHENOL; NIACINAMIDE; GUAR GUM; PEG-40 CASTOR OIL; CITRIC ACID MONOHYDRATE; SODIUM HYDROXIDE

DOUXO S3™ CALM

mousse

OPHYTRIUM 0.75%

Soap, sulfate, paraben, phthalate, colorant and nanoparticle FREE

Leave-on for longer lasting action. High tolerance formula. Hypoallergenic fragrance, adjusted pH. Formulated and tested by veterinary dermatology experts.

ACTIVE INGREDIENT: Ophytrium 0.75%

INACTIVE INGREDIENT

INACTIVE INGREDIENTS: Water, capryl/capramidopropyl betaine, phenoxyethanol, pentavitin® (saccharide isomerate), panthenol, niacinamide (vit. PP), coco+vanilla hypoallergenic fragrance, guar gum, PEG-40 hydrogenated castor oil, citric acid, sodium hydroxide.

DESCRIPTION

PROPERTIES: Ophytrium is a purified, natural ingredient from the S3 - Safe Skincare Selection. Ophytrium has been carefully selected for its high tolerance and simultaneous threefold action on the skin’s ecosystem: • Helps support the skin's physical barrier for supple, hydrated skin • Helps support the microbial flora for healthy skin • Helps soothe irritated skin

INDICATIONS AND USAGE

INDICATIONS: For use on dogs or cats with itchy, irritated or allergic skin. Helps soothe while hydrating the skin. Detangles the fur and leaves the coat soft and shiny.

DIRECTIONS: Apply to a brushed, dry coat. First, gently massage onto the problem area until the mousse reaches the skin. Repeat this action all over the body, avoiding the eyes and mouth. Let air dry. Brush for a shiny coat. Wash hands after use. Use DOUXO® S3 CALM Shampoo to clean the skin if needed.

PRECAUTIONS

CAUTION: For external use on dogs or cats only. Avoid contact with eyes. If eye contact occurs, rinse thoroughly and consult your veterinarian. If skin irritation occurs or increases, discontinue use and consult with your veterinarian. Keep out of reach of children.

STORAGE AND HANDLING

Store at room temperature.

“How to use” video www.douxo.com

Manufactured for Ceva Animal Health, LLC, Lenexa, KS 66215, 800-999-0297
Pentavitin® is a registered trademark of DSMP Assets B.V.
All other trademarks are owned by Ceva Santé Animale S.A. or its affiliates.

PRINCIPAL DISPLAY PANEL - 200 mL Bottle

DOUXO S3™

CALM

OPHYTRIUM 0.75%

soothing

ITCHY, IRRITATED SKIN

mousse

leave-on

For use on dogs or cats

5 fl oz (150 mL)